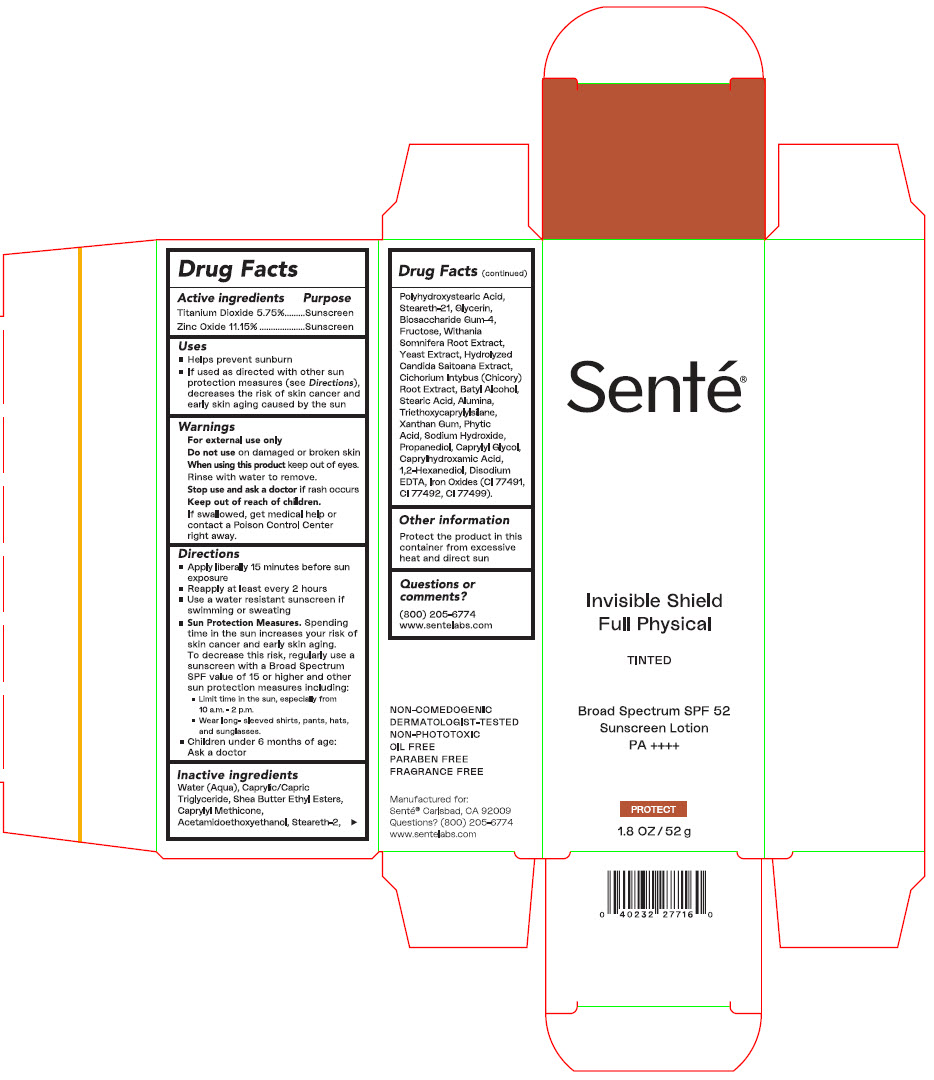 DRUG LABEL: Invisible Shield Full Physical Tinted SPF 52 Broad Spectrum Sunscreen
NDC: 71398-012 | Form: LOTION
Manufacturer: SENTÉ, Inc.
Category: otc | Type: HUMAN OTC DRUG LABEL
Date: 20240404

ACTIVE INGREDIENTS: Titanium Dioxide 57.5 mg/1 g; Zinc Oxide 111.5 mg/1 g
INACTIVE INGREDIENTS: Water; Medium-Chain Triglycerides; Caprylyl Trisiloxane; Steareth-2; POLYHYDROXYSTEARIC ACID (2300 MW); Steareth-21; Glycerin; Biosaccharide Gum-4; Fructose; Withania Somnifera Root; Yeast, Unspecified; CICHORIUM INTYBUS (CHICORY) ROOT OLIGOSACCHARIDES; Batilol; Stearic Acid; Aluminum Oxide; Triethoxycaprylylsilane; Xanthan Gum; Fytic Acid; Propanediol; Caprylyl Glycol; Caprylhydroxamic Acid; 1,2-Hexanediol; Edetate Disodium; Ferrosoferric Oxide; Ferric Oxide Red; Ferric Oxide Yellow; Sodium Hydroxide

Invisible Shield Full Physical Tinted SPF 52 Broad Spectrum Sunscreen

Drug Facts

ACTIVE INGREDIENT

Active ingredients | Purpose
Titanium Dioxide 5.75% | Sunscreen
Zinc Oxide 11.15% | Sunscreen

Uses

- Helps prevent sunburn
- If used as directed with other sun protection measures (see Directions), decreases the risk of skin cancer and early skin aging caused by the sun

Warnings

For external use only

Do not use on damaged or broken skin

When using this product keep out of eyes. Rinse with water to remove.

Stop use and ask a doctor if rash occurs

Keep out of reach of children.

If swallowed, get medical help or contact a Poison Control Center right away.

Directions

- Apply liberally 15 minutes before sun exposure
- Reapply at least every 2 hours
- Use a water resistant sunscreen if swimming or sweating
- Sun Protection Measures. Spending time in the sun increases your risk of skin cancer and early skin aging. To decrease this risk, regularly use a sunscreen with a Broad Spectrum SPF value of 15 or higher and other sun protection measures including:
  - Limit time in the sun, especially from 10 a.m.-2 p.m.
  - Wear long- sleeved shirts, pants, hats, and sunglasses.
- Children under 6 months of age: Ask a doctor

Inactive ingredients

Water (Aqua), Caprylic/Capric Triglyceride, Shea Butter Ethyl Esters, Caprylyl Methicone, Acetamidoethoxyethanol, Steareth-2, Polyhydroxystearic Acid, Steareth-21, Glycerin, Biosaccharide Gum-4, Fructose, Withania Somnifera Root Extract, Yeast Extract, Hydrolyzed Candida Saitoana Extract, Cichorium Intybus (Chicory) Root Extract, Batyl Alcohol, Stearic Acid, Alumina, Triethoxycaprylylsilane, Xanthan Gum, Phytic Acid, Sodium Hydroxide, Propanediol, Caprylyl Glycol, Caprylhydroxamic Acid, 1,2-Hexanediol, Disodium EDTA, Iron Oxides (CI 77491, CI 77492, CI 77499)

Other information

Protect the product in this container from excessive heat and direct sun

Questions or comments?

(800) 205-6774

www.sentelabs.com

PRINCIPAL DISPLAY PANEL - 52 g Tube Carton

Senté®

Invisible Shield
Full Physical

TINTED

Broad Spectrum SPF 52
Sunscreen Lotion
PA ++++

PROTECT

1.8 OZ/52 g